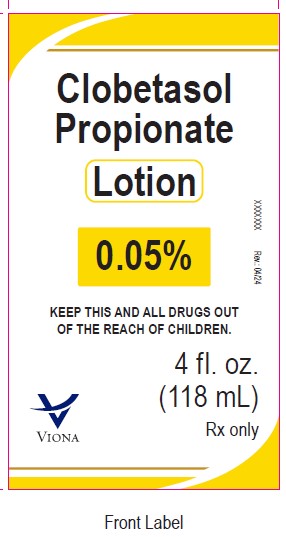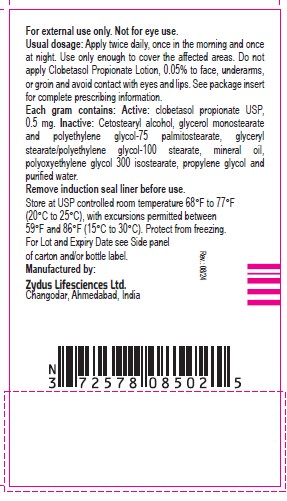 DRUG LABEL: Clobetasol Propionate
NDC: 70771-1498 | Form: LOTION
Manufacturer: Zydus Lifesciences Limited
Category: prescription | Type: HUMAN PRESCRIPTION DRUG LABEL
Date: 20240814

ACTIVE INGREDIENTS: CLOBETASOL PROPIONATE 0.05 g/100 mL
INACTIVE INGREDIENTS: CETOSTEARYL ALCOHOL; GLYCERYL MONOSTEARATE; PEG-100 STEARATE; GLYCERYL STEARATE/PEG-100 STEARATE; MINERAL OIL; PEG-6 ISOSTEARATE; PROPYLENE GLYCOL; WATER

CLOBETASOL PROPIONATE lotion, 0.05%

PACKAGE LABEL.PRINCIPAL DISPLAY PANEL

NDC 70771-1498-7

Clobetasol Propionate Lotion, 0.05%

Rx only

118 mL